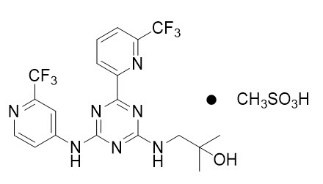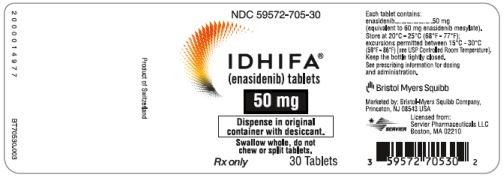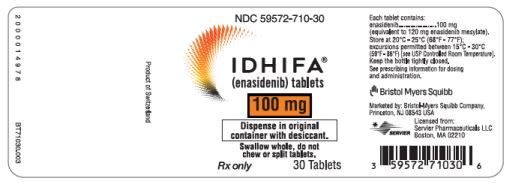 DRUG LABEL: Idhifa
NDC: 59572-705 | Form: TABLET, FILM COATED
Manufacturer: Celgene Corporation
Category: prescription | Type: HUMAN PRESCRIPTION DRUG LABEL
Date: 20250116

ACTIVE INGREDIENTS: ENASIDENIB MESYLATE 50 mg/1 1
INACTIVE INGREDIENTS: MICROCRYSTALLINE CELLULOSE; HYDROXYPROPYL CELLULOSE, UNSPECIFIED; SODIUM STARCH GLYCOLATE TYPE A POTATO; SODIUM LAURYL SULFATE; HYPROMELLOSE ACETATE SUCCINATE 06081224 (3 MPA.S); SILICON DIOXIDE; MAGNESIUM STEARATE; POLYVINYL ALCOHOL, UNSPECIFIED; TITANIUM DIOXIDE; POLYETHYLENE GLYCOL, UNSPECIFIED; TALC; FERRIC OXIDE YELLOW

HIGHLIGHTS OF PRESCRIBING INFORMATION

These highlights do not include all the information needed to use IDHIFA safely and effectively. See full prescribing information for IDHIFA.
IDHIFA® (enasidenib) tablets, for oral use
Initial U.S. Approval: 2017

WARNING: DIFFERENTIATION SYNDROME

See full prescribing information for complete boxed warning.

Patients treated with IDHIFA have experienced symptoms of differentiation syndrome, which can be fatal if not treated. If differentiation syndrome is suspected, initiate corticosteroid therapy and hemodynamic monitoring until symptom resolution (5.1, 6.1).

1 INDICATIONS AND USAGE

IDHIFA is an isocitrate dehydrogenase-2 inhibitor indicated for the treatment of adult patients with relapsed or refractory acute myeloid leukemia (AML) with an isocitrate dehydrogenase-2 (IDH2) mutation as detected by an FDA-approved test (1.1).

2 DOSAGE AND ADMINISTRATION

100 mg orally once daily until disease progression or unacceptable toxicity (2.2).

3 DOSAGE FORMS AND STRENGTHS

Tablets: 50 mg or 100 mg (3).

4 CONTRAINDICATIONS

None (4).

5 WARNINGS AND PRECAUTIONS

Embryo-Fetal Toxicity: IDHIFA can cause fetal harm. Advise patients of the potential risk to a fetus and use effective contraception (5.2, 8.1, 8.3).

6 ADVERSE REACTIONS

The most common adverse reactions (≥20%) are nausea, vomiting, diarrhea, elevated bilirubin, and decreased appetite (6.1).

To report SUSPECTED ADVERSE REACTIONS, contact Bristol Myers Squibb at 1-800-721-5072 or FDA at 1-800-FDA-1088 or www.fda.gov/medwatch.

7 DRUG INTERACTIONS

- Certain CYP1A2 and CYP2C19 Substrates: Avoid concomitant use unless otherwise recommended in the Prescribing Information (7.1).
- Certain CYP3A Substrates: Avoid concomitant use unless otherwise recommended in the Prescribing Information (7.1).
- Certain OATP1B1, OATP1B3, and BCRP Substrates: Avoid concomitant use unless otherwise recommended in the Prescribing Information (7.1).

8 USE IN SPECIFIC POPULATIONS

Lactation: Advise not to breastfeed (8.2).

FULL PRESCRIBING INFORMATION

WARNING: DIFFERENTIATION SYNDROME

Patients treated with IDHIFA have experienced symptoms of differentiation syndrome, which can be fatal if not treated. Symptoms may include fever, dyspnea, acute respiratory distress, pulmonary infiltrates, pleural or pericardial effusions, rapid weight gain or peripheral edema, lymphadenopathy, bone pain, and hepatic, renal, or multi-organ dysfunction. If differentiation syndrome is suspected, initiate corticosteroid therapy and hemodynamic monitoring until symptom resolution [see Warnings and Precautions (5.1) and Adverse Reactions (6.1)].

1 INDICATIONS AND USAGE

1.1 Acute Myeloid Leukemia

IDHIFA is indicated for the treatment of adult patients with relapsed or refractory acute myeloid leukemia (AML) with an isocitrate dehydrogenase-2 (IDH2) mutation as detected by an FDA-approved test.

2 DOSAGE AND ADMINISTRATION

2.1 Patient Selection

Select patients for the treatment of AML with IDHIFA based on the presence of IDH2 mutations in the blood or bone marrow [see Indications and Usage (1.1) and Clinical Studies (14.1)]. Information on FDA-approved tests for the detection of IDH2 mutations in AML is available at http://www.fda.gov/CompanionDiagnostics.

2.2 Recommended Dosage

The recommended dosage of IDHIFA is 100 mg taken orally once daily with or without food until disease progression or unacceptable toxicity. For patients without disease progression or unacceptable toxicity, treat for a minimum of 6 months to allow time for clinical response.

Swallow tablets whole. Do not chew, split, or crush IDHIFA tablets. Administer IDHIFA tablets orally about the same time each day. If a dose of IDHIFA is vomited, missed, or not taken at the usual time, administer the dose as soon as possible on the same day, and return to the normal schedule the following day.

2.3 Monitoring and Dosage Modifications for Toxicities

Assess blood counts and blood chemistries for leukocytosis and tumor lysis syndrome prior to the initiation of IDHIFA and monitor at a minimum of every 2 weeks for at least the first 3 months during treatment. Manage any abnormalities promptly [see Adverse Reactions (6.1)].

Interrupt dosing or reduce dose for toxicities. See Table 1 for dosage modification guidelines.

Table 1: Dosage Modifications for IDHIFA-Related Toxicities
Adverse Reaction | Recommended Action
- Differentiation syndrome | - If differentiation syndrome is suspected, administer systemic corticosteroids and initiate hemodynamic monitoring [see Warnings and Precautions (5.1)]. - Interrupt IDHIFA if severe pulmonary symptoms requiring intubation or ventilator support, and/or renal dysfunction persist for more than 48 hours after initiation of corticosteroids [see Warnings and Precautions (5.1)]. - Resume IDHIFA when signs and symptoms improve to Grade 2* or lower.
- Noninfectious leukocytosis (white blood cell [WBC] count greater than 30 × 10^9/L) | - Initiate treatment with hydroxyurea, as per standard institutional practices. - Interrupt IDHIFA if leukocytosis is not improved with hydroxyurea, and then resume IDHIFA at 100 mg daily when WBC is less than 30 × 10^9/L.
- Elevation of bilirubin greater than 3 times the upper limit of normal (ULN) sustained for ≥2 weeks without elevated transaminases or other hepatic disorders | - Reduce IDHIFA dose to 50 mg daily. - Resume IDHIFA at 100 mg daily if bilirubin elevation resolves to less than 2 × ULN.
- Other Grade 3* or higher toxicity considered related to treatment including tumor lysis syndrome | - Interrupt IDHIFA until toxicity resolves to Grade 2* or lower. - Resume IDHIFA at 50 mg daily; may increase to 100 mg daily if toxicities resolve to Grade 1* or lower. - If Grade 3* or higher toxicity recurs, discontinue IDHIFA.
*Grade 1 is mild, Grade 2 is moderate, Grade 3 is serious, Grade 4 is life-threatening.

3 DOSAGE FORMS AND STRENGTHS

IDHIFA is available in the following tablet strengths:

- 50 mg enasidenib tablet: Pale yellow to yellow oval-shaped film-coated tablet debossed "ENA" on one side and "50" on the other side.
- 100 mg enasidenib tablet: Pale yellow to yellow capsule-shaped film-coated tablet debossed "ENA" on one side and "100" on the other side.

4 CONTRAINDICATIONS

None.

5 WARNINGS AND PRECAUTIONS

5.1 Differentiation Syndrome

In the clinical trial, 14% of patients treated with IDHIFA experienced differentiation syndrome, which may be life-threatening or fatal if not treated. Differentiation syndrome is associated with rapid proliferation and differentiation of myeloid cells. While there is no diagnostic test for differentiation syndrome, symptoms in patients treated with IDHIFA included acute respiratory distress represented by dyspnea and/or hypoxia (68%) and need for supplemental oxygen (76%); pulmonary infiltrates (73%) and pleural effusion (45%); renal impairment (70%); fever (36%); lymphadenopathy (33%); bone pain (27%); peripheral edema with rapid weight gain (21%); and pericardial effusion (18%). Hepatic, renal, and multi-organ dysfunction have also been observed.

Differentiation syndrome has been observed with and without concomitant hyperleukocytosis, in as early as 1 day and up to 5 months after IDHIFA initiation.

If differentiation syndrome is suspected, initiate oral or intravenous corticosteroids (e.g., dexamethasone 10 mg every 12 hours) and hemodynamic monitoring until improvement. Taper corticosteroids only after resolution of symptoms. Symptoms of differentiation syndrome may recur with premature discontinuation of corticosteroid treatment. If severe pulmonary symptoms requiring intubation or ventilator support, and/or renal dysfunction persist for more than 48 hours after initiation of corticosteroids, interrupt IDHIFA until signs and symptoms are no longer severe [see Dosage and Administration (2.3)]. Hospitalization for close observation and monitoring of patients with pulmonary and/or renal manifestation is recommended.

5.2 Embryo-Fetal Toxicity

Based on animal embryo-fetal toxicity studies, IDHIFA can cause embryo-fetal harm when administered to a pregnant woman. In animal embryo-fetal toxicity studies, enasidenib caused embryo-fetal toxicities starting at 0.1 times the steady state clinical exposure based on the area under the concentration-time curve (AUC) at the recommended human dose.

Advise pregnant women of the potential risk to the fetus. Advise females of reproductive potential to use effective non‑hormonal contraception during treatment with IDHIFA and for 2 months after the last dose. Advise males with female partners of reproductive potential to use effective contraception during treatment with IDHIFA and for 2 months after the last dose [see Use in Specific Populations (8.1, 8.3)].

6 ADVERSE REACTIONS

The following clinically significant adverse reactions are described elsewhere in the labeling:

- Differentiation Syndrome [see Warnings and Precautions (5.1)]

6.1 Clinical Trials Experience

Because clinical trials are conducted under widely varying conditions, adverse reaction rates observed in the clinical trials of a drug cannot be directly compared to rates in the clinical trials of another drug and may not reflect the rates observed in practice.

The safety evaluation of single-agent IDHIFA is based on 214 patients with relapsed or refractory AML who were assigned to receive 100 mg daily [see Clinical Studies (14.1)]. The median duration of exposure to IDHIFA was 4.3 months (range 0.3 to 23.6). The 30-day and 60-day mortality rates observed with IDHIFA were 4.2% (9/214) and 11.7% (25/214), respectively.

Serious adverse reactions were reported in 77.1% of patients. The most frequent serious adverse reactions (≥2%) were leukocytosis (10%), diarrhea (6%), nausea (5%), vomiting (3%), decreased appetite (3%), tumor lysis syndrome (5%), and differentiation syndrome (8%). Differentiation syndrome events characterized as serious included pyrexia, renal failure acute, hypoxia, respiratory failure, and multi-organ failure.

Overall, 92 of 214 patients (43%) required a dose interruption due to an adverse reaction; the most frequent adverse reactions leading to dose interruption were differentiation syndrome (4%) and leukocytosis (3%). Ten of 214 patients (5%) required a dose reduction due to an adverse reaction; no adverse reaction required dose reduction in more than 2 patients. Thirty-six of 214 patients (17%) permanently discontinued IDHIFA due to an adverse reaction; the most frequent adverse reaction leading to permanent discontinuation was leukocytosis (1%).

The most common adverse reactions (≥20%) of any grade were nausea, vomiting, diarrhea, elevated bilirubin and decreased appetite.

Adverse reactions reported in the trial are shown in Table 2.

Table 2: Adverse Reactions Reported in ≥10% (Any Grade) or ≥3% (Grade 3-5) of Patients with Relapsed or Refractory AML
 | IDHIFA (100 mg daily) N=214
Body System Adverse Reaction | All Grades N=214 n (%) | ≥Grade 3 N=214 n (%)
Gastrointestinal Disordersa
Nausea | 107 (50) | 11 (5)
Diarrhea | 91 (43) | 17 (8)
Vomiting | 73 (34) | 4 (2)
Metabolism and Nutrition Disorders
Decreased appetite | 73 (34) | 9 (4)
Tumor lysis syndromeb | 13 (6) | 12 (6)
Blood and Lymphatic System Disorders
Differentiation syndromec | 29 (14) | 15 (7)
Noninfectious leukocytosis | 26 (12) | 12 (6)
Nervous System Disorders
Dysgeusia | 25 (12) | 0 (0)
a Gastrointestinal disorders observed with IDHIFA treatment can be associated with other commonly reported events such as abdominal pain, and weight decreased.
b Tumor lysis syndrome observed with IDHIFA treatment can be associated with commonly reported uric acid increased.
c Differentiation syndrome can be associated with other commonly reported events such as respiratory failure, dyspnea, hypoxia, pyrexia, peripheral edema, rash, or renal insufficiency.

Other clinically significant adverse reactions occurring in <10% of patients included:

- Respiratory, Thoracic, and Mediastinal Disorders: Pulmonary edema, acute respiratory distress syndrome

Changes in selected post-baseline laboratory values that were observed in patients with relapsed or refractory AML are shown in Table 3.

Table 3: Most Common (≥20%) New or Worsening Laboratory Abnormalities Reported in Patients with Relapsed or Refractory AML
 | IDHIFA (100 mg daily) N=214
Parametera | All Grades (%) | Grade ≥3 (%)
Total bilirubin increased | 81 | 15
Calcium decreased | 74 | 8
Potassium decreased | 41 | 15
Phosphorus decreased | 27 | 8
a Includes abnormalities occurring up to 28 days after last IDHIFA dose, if new or worsened by at least one grade from baseline, or if baseline was unknown. The denominator varies based on data collected for each parameter (N=213 except phosphorous N=209).

Elevated Bilirubin

IDHIFA may interfere with bilirubin metabolism through inhibition of UGT1A1 [see Clinical Pharmacology (12.3)]. Thirty-seven percent of patients (80/214) experienced total bilirubin elevations ≥2 x ULN at least one time. Of those patients who experienced total bilirubin elevations ≥2 x ULN, 35% had elevations within the first month of treatment, and 89% had no concomitant elevation of transaminases or other severe adverse events related to liver disorders. No patients required a dose reduction for hyperbilirubinemia; treatment was interrupted in 3.7% of patients, for a median of 6 days. Three patients (1.4%) discontinued IDHIFA permanently due to hyperbilirubinemia.

Noninfectious Leukocytosis

IDHIFA can induce myeloid proliferation resulting in a rapid increase in white blood cell count.

Tumor Lysis Syndrome

IDHIFA can induce myeloid proliferation resulting in a rapid reduction in tumor cells which may pose a risk for tumor lysis syndrome.

Other Clinical Trials Experience

The following adverse reactions occurred in other clinical trials of IDHIFA at the recommended dosage: neutropenia, thrombocytopenia, anemia, stomatitis, renal failure, fatigue, dyspnea, and QT prolongation.

7 DRUG INTERACTIONS

7.1 Effect of IDHIFA on Other Drugs

Certain CYP1A2 Substrates

Avoid concomitant use with IDHIFA unless otherwise recommended in the Prescribing Information for CYP1A2 substrates where minimal concentration changes may lead to serious adverse reactions. Consider reducing the frequency of caffeine intake from various food and beverages in a 24 hour period while taking IDHIFA because IDHIFA may increase the effect of caffeine in patients who are sensitive to it.

Enasidenib is a CYP1A2 inhibitor. Concomitant use of IDHIFA increases the exposure of CYP1A2 substrates [see Clinical Pharmacology (12.3)], which may increase the risk of adverse reactions related to the substrates.

Certain CYP2C19 substrates

Avoid concomitant use with IDHIFA unless otherwise recommended in the Prescribing Information for CYP2C19 substrates where minimal concentration changes may lead to serious adverse reactions.

Enasidenib is a CYP2C19 inhibitor. Concomitant use of IDHIFA increases the exposure of CYP2C19 substrates [see Clinical Pharmacology (12.3)], which may increase the risk of adverse reactions related to these substrates.

Certain CYP3A substrates

Avoid concomitant use with IDHIFA unless otherwise recommended in the Prescribing Information for CYP3A substrates where minimal concentration changes may lead to reduced efficacy.

Do not administer IDHIFA with anti-fungal agents that are substrates of CYP3A due to expected loss of antifungal efficacy.

Co-administration of IDHIFA may decrease the concentrations of hormonal contraceptives. Consider alternative methods of contraception in patients receiving IDHIFA [See use in Specific Population (8.1, 8.3)].

Enasidenib is a CYP3A inducer. Concomitant use of IDHIFA decreases the exposure of CYP3A substrates [see Clinical Pharmacology (12.3)], which may reduce the efficacy of the substrates.

Certain OATP1B1, OATP1B3, and BCRP Substrates

Avoid coadministration of IDHIFA with OATP1B1, OATP1B3, and BCRP substrates, for which minimal concentration changes may lead to serious toxicities. If coadministration cannot be avoided, decrease the OATP1B1, OATP1B3, and BCRP substrates dosage(s) in accordance with the respective Prescribing Information.

Enasidenib is an OATP1B1, OATP1B3, and BCRP transporter inhibitor. Concomitant use of IDHIFA increases the exposure of OATP1B1, OATP1B3, and BCRP substrates [see Clinical Pharmacology (12.3)], which may increase the risk of adverse reactions related to these substrates.

Certain P-glycoprotein (P-gp) Substrates

When coadministered with IDHIFA, follow recommended P-gp substrates Prescribing Information and monitor more frequently for adverse reactions related to these substrates.

Enasidenib is a P-gp transporter inhibitor. Concomitant use of IDHIFA increases the exposure of P-gp substrates [see Clinical Pharmacology (12.3)], which may increase the risk of adverse reactions related to the substrates.

8 USE IN SPECIFIC POPULATIONS

8.1 Pregnancy

Risk Summary

Based on animal embryo-fetal toxicity studies, IDHIFA can cause fetal harm when administered to a pregnant woman. There are no available data on IDHIFA use in pregnant women to inform a drug-associated risk of major birth defects and miscarriage. In animal embryo-fetal toxicity studies, oral administration of enasidenib to pregnant rats and rabbits during organogenesis was associated with embryo-fetal mortality and alterations to growth starting at 0.1 times the steady state clinical exposure based on the AUC at the recommended human dose (see Data). Advise pregnant women of the potential risk to a fetus.

In the U.S. general population, the estimated background risk of major birth defects and miscarriage in clinically recognized pregnancies is 2%-4% and 15%-20%, respectively.

Data

Animal Data

Enasidenib administered to pregnant rats at a dose of 30 mg/kg twice daily during organogenesis (gestation days 6-17) was associated with maternal toxicity and adverse embryo-fetal effects including post-implantation loss, resorptions, decreased viable fetuses, lower fetal birth weights, and skeletal variations. These effects occurred in rats at approximately 1.6 times the clinical exposure at the recommended human daily dose of 100 mg/day.

In pregnant rabbits treated during organogenesis (gestation days 7-19), enasidenib was maternally toxic at doses equal to 5 mg/kg/day or higher (exposure approximately 0.1 to 0.6 times the steady state clinical exposure at the recommended daily dose) and caused spontaneous abortions at 5 mg/kg/day (exposure approximately 0.1 times the steady state clinical exposure at the recommended daily dose).

8.2 Lactation

Risk Summary

There are no data on the presence of enasidenib or its metabolites in human milk, the effects on the breastfed child, or the effects on milk production. Because of the potential for adverse reactions in the breastfed child, advise women not to breastfeed during treatment with IDHIFA and for 2 months after the last dose.

8.3 Females and Males of Reproductive Potential

Based on animal embryo-fetal toxicity studies, IDHIFA can cause fetal harm when administered to a pregnant woman [see Use in Specific Populations (8.1)].

Pregnancy Testing

Verify pregnancy status in females of reproductive potential prior to starting IDHIFA.

Contraception

Females

Advise females of reproductive potential to use effective contraception during treatment with IDHIFA and for 2 months after the last dose. Coadministration of IDHIFA may decrease the concentrations of combined hormonal contraceptives. Advise patients using hormonal contraceptives to use an effective non-hormonal contraceptive method during treatment with IDHIFA and for 2 months after the last dose [see Drug Interactions (7.1)].

Males

Advise males with female partners of reproductive potential to use effective contraception during treatment with IDHIFA and for 2 months after the last dose of IDHIFA.

Infertility

Based on findings in animals, IDHIFA may impair fertility in females and males of reproductive potential. It is not known whether these effects on fertility are reversible [see Nonclinical Toxicology (13.1)].

8.4 Pediatric Use

Safety and effectiveness of IDHIFA in pediatric patients have not been established.

8.5 Geriatric Use

No dosage adjustment is required for IDHIFA based on age. In the clinical study, 61% of 214 patients were aged 65 years or older, while 24% were older than 75 years. No overall differences in effectiveness or safety were observed between patients aged 65 years or older and younger patients.

11 DESCRIPTION

Enasidenib is an inhibitor of isocitrate dehydrogenase-2 (IDH2) enzyme. Enasidenib is available as the mesylate salt with the chemical name:

2-methyl-1-[(4-[6-(trifluoromethyl)pyridin-2-yl]-6-{[2-(trifluoromethyl)pyridin-4-yl]amino}-1,3,5-triazin-2-yl)amino]propan-2-ol methanesulfonate.

Or

2-Propanol, 2-methyl-1-[[4-[6-(trifluoromethyl)-2-pyridinyl]-6-[[2-(trifluoromethyl)-4-pyridinyl]amino-1,3,5-triazin-2-yl]amino]-, methanesulfonate (1:1).

The chemical structure is:

The empirical formula is C19H17F6N7O ∙ CH3SO3H (C20H21F6N7O4S), and the molecular weight is 569.48 g/mol. Enasidenib is practically insoluble (solubility ≤74 mcg/mL) in aqueous solutions across physiological pH range (pH 1.2 and 7.4).

IDHIFA (enasidenib) is available as a 50 mg tablet (equivalent to 60 mg enasidenib mesylate) and a 100 mg tablet (equivalent to 120 mg enasidenib mesylate) for oral administration. Each tablet contains inactive ingredients of colloidal silicon dioxide, hydroxypropyl cellulose, hypromellose acetate succinate, iron oxide yellow, magnesium stearate, microcrystalline cellulose, polyethylene glycol, polyvinyl alcohol, sodium lauryl sulfate, sodium starch glycolate, talc, and titanium dioxide.

12 CLINICAL PHARMACOLOGY

12.1 Mechanism of Action

Enasidenib is a small molecule inhibitor of the isocitrate dehydrogenase 2 (IDH2) enzyme. Enasidenib targets the mutant IDH2 variants R140Q, R172S, and R172K at approximately 40-fold lower concentrations than the wild-type enzyme in vitro. Inhibition of the mutant IDH2 enzyme by enasidenib led to decreased 2-hydroxyglutarate (2-HG) levels and induced myeloid differentiation in vitro and in vivo in mouse xenograft models of IDH2 mutated AML. In blood samples from patients with AML with mutated IDH2, enasidenib decreased 2-HG levels, reduced blast counts and increased percentages of mature myeloid cells.

12.2 Pharmacodynamics

Cardiac Electrophysiology

The potential for QTc prolongation with enasidenib was evaluated in an open-label study in patients with advanced hematologic malignancies with an IDH2 mutation. No large mean changes in the QTc interval (>20 ms) were observed following treatment with enasidenib.

12.3 Pharmacokinetics

The peak plasma concentration (Cmax) is 1.4 mcg/mL [coefficient of variation (CV%) 50%] after a single dose of 100 mg, and 13.1 mcg/mL (CV% 45%) at steady state for 100 mg daily. The area under concentration time curve (AUC) of enasidenib increases in an approximately dose proportional manner from 50 mg (0.5 times approved recommended dosage) to 450 mg (4.5 times approved recommended dosage) daily dose. Steady-state plasma levels are reached within 29 days of once-daily dosing. Accumulation is approximately 10-fold when administered once daily.

Absorption

The absolute bioavailability after 100 mg oral dose of enasidenib is approximately 57%. After a single oral dose, the median time to Cmax (Tmax) is 4 hours.

Distribution

The mean volume of distribution (Vd) of enasidenib is 55.8 L (CV% 29). Human plasma protein binding of enasidenib is 98.5% and of its metabolite AGI-16903 is 96.6% in vitro.

Elimination

Enasidenib has a terminal half-life of 7.9 days and a mean total body clearance (CL/F) of 0.70 L/hour (CV% 62.5).

Metabolism

Enasidenib accounted for 89% of the radioactivity in circulation and AGI-16903, the N-dealkylated metabolite, represented 10% of the circulating radioactivity.

Metabolism of enasidenib is mediated by multiple cytochrome P450 (CYP) enzymes (e.g., CYP1A2, CYP2B6, CYP2C8, CYP2C9, CYP2C19, CYP2D6, and CYP3A4), and by multiple UDP glucuronosyl transferases (UGTs) (e.g., UGT1A1, UGT1A3, UGT1A4, UGT1A9, UGT2B7, and UGT2B15) in vitro. Further metabolism of the metabolite AGI-16903 is also mediated by multiple enzymes (e.g., CYP1A2, CYP2C19, CYP3A4, UGT1A1, UGT1A3, and UGT1A9) in vitro.

Excretion

Eighty-nine percent (89%) of enasidenib is eliminated in feces and 11% in the urine. Excretion of unchanged enasidenib accounts for 34% of the radiolabeled drug in the feces and 0.4% in the urine.

Specific Populations

No clinically meaningful effect on the pharmacokinetics of enasidenib was observed for the following covariates: age (19 years to 100 years), race (White, Black, or Asian), mild (Child-Pugh A or total bilirubin ≤upper limit of normal (ULN) and aspartate transaminase (AST) >ULN or total bilirubin 1 to 1.5 times ULN and any AST), moderate (Child-Pugh B or total bilirubin >1.5 to 3 times ULN and any AST), and severe (Child-Pugh C or total bilirubin >3 to 10 times ULN and any AST) hepatic impairment, renal impairment (defined as creatinine clearance ≥30 mL/min by Cockcroft-Gault formula), sex, body weight (39 kg to 136 kg), and body surface area.

Drug Interaction Studies

Clinical Studies

CYP1A2 Substrates: Caffeine (a sensitive CYP1A2 substrate) AUC0-INF and Cmax increased by 655% and 18%, respectively, following concomitant use of multiple doses of IDHIFA 100 mg with a single oral dose of 100 mg caffeine.

CYP2C19 substrates: Omeprazole (a sensitive CYP2C19 substrate) AUC0-INF and Cmax increased by 86% and 47%, respectively, following concomitant use of multiple doses of IDHIFA 100 mg with a single oral dose of omeprazole 40 mg.

CYP2D6 substrates: Dextromethorphan (a sensitive CYP2D6 substrate) AUC0-INF and Cmax increased by 37% and 24% respectively, following concomitant use of multiple doses of IDHIFA 100 mg with a single oral dose of dextromethorphan 30 mg.

CYP3A substrates: Midazolam (a sensitive CYP3A substrate) AUC0‑INF and Cmax decreased by 43% and 23%, respectively, following concomitant use of multiple doses of IDHIFA 100 mg with a single intravenous dose of midazolam 0.03 mg/kg. The decrease in midazolam exposure following oral administration of midazolam is expected to be larger than that following intravenous administration of midazolam. This is due to induction of CYP3A4 first pass metabolism by enasidenib and the reduced bioavailability of the midazolam oral formulation compared to the midazolam intravenous formulation.

CYP2C9 and CYP2C8 substrates: Coadministration of multiple doses of IDHIFA 100 mg did not have clinically significant effect on the exposure of flurbiprofen (a CYP2C9 substrate) or pioglitazone (a CYP2C8 substrate).

OATP1B1, OATP1B3, and BCRP Substrates: Rosuvastatin (an OATP1B1, OATP1B3, and BCRP substrate) AUC0-INF and Cmax increased by 244% and 366%, respectively, following concomitant use of multiple doses of IDHIFA 100 mg with a single oral dose of rosuvastatin 10 mg.

P-gp Substrates: Digoxin (a P-gp Substrate) AUC0-30h and Cmax increased by 20% and 26%, respectively, following concomitant use of multiple doses of IDHIFA 100 mg with a single oral dose of digoxin 0.25 mg.

In Vitro Studies

CYP and UGT Enzymes: Enasidenib inhibits CYP2B6 and UGT1A1. The metabolite AGI-16903 inhibits CYP1A2, CYP2B6, CYP2C8, CYP2C9, CYP2C19, and CYP2D6. Enasidenib induces CYP2B6.

Transporter Systems: Enasidenib is not a substrate for P-glycoprotein (P-gp) or breast cancer resistance protein (BCRP). AGI-16903 is a substrate of both P-gp and BCRP. Enasidenib and AGI-16903 are not substrates of multidrug resistance-associated protein 2 (MRP2), organic anion transporter 1 (OAT1), OAT3, organic anion transporter family member 1B1 (OATP1B1), OATP1B3, and organic cation transporter 2 (OCT2).

Enasidenib inhibits OAT1 and OCT2, but not MRP2 or OAT3. AGI-16903 inhibits BCRP, OAT1, OAT3, OATP1B1, and OCT2, but not P-gp, MRP2, or OATP1B3.

13 NONCLINICAL TOXICOLOGY

13.1 Carcinogenesis, Mutagenesis, Impairment of Fertility

Carcinogenicity studies have not been performed with enasidenib.

Enasidenib was not mutagenic in an in vitro bacterial reverse mutation (Ames) assay. Enasidenib was not clastogenic in an in vitro human lymphocyte chromosomal aberration assay, or in an in vivo rat bone marrow micronucleus assay.

Fertility studies in animals have not been conducted with enasidenib. In repeat-dose toxicity studies with twice daily oral administration of enasidenib in rats up to 90-days in duration, changes were reported in male and female reproductive organs including seminiferous tubular degeneration, hypospermia, atrophy of the seminal vesicle and prostate, decreased corpora lutea and increased atretic follicles in the ovaries, and atrophy in the uterus.

14 CLINICAL STUDIES

14.1 Acute Myeloid Leukemia

The efficacy of IDHIFA was evaluated in an open-label, single-arm, multicenter, two-cohort clinical trial (Study AG221-C-001, NCT01915498) of 199 adult patients with relapsed or refractory AML and an IDH2 mutation, who were assigned to receive 100 mg daily dose. Cohort 1 included 101 patients and Cohort 2 included 98 patients. IDH2 mutations were identified by a local diagnostic test and retrospectively confirmed by the Abbott RealTime IDH2 assay, or prospectively identified by the Abbott RealTime IDH2 assay, which is the FDA-approved test for selection of patients with AML for treatment with IDHIFA. IDHIFA was given orally at starting dose of 100 mg daily until disease progression or unacceptable toxicity. Dose reductions were allowed to manage adverse events.

The baseline demographic and disease characteristics are shown in Table 4. The baseline demographics and disease characteristics were similar in both study cohorts.

Table 4: Baseline Demographic and Disease Characteristics in Patients with Relapsed or Refractory AML
Demographic and Disease Characteristics | IDHIFA (100 mg daily) N=199
Demographics
Age (Years) Median (Min, Max) | 68 (19, 100)
Age Categories, n (%)
<65 years | 76 (38)
≥65 years to <75 years | 74 (37)
≥75 years | 49 (25)
Sex, n (%)
Male | 103 (52)
Female | 96 (48)
Race, n (%)
White | 153 (77)
Black | 10 (5)
Asian | 1 (1)
Native Hawaiian/Other Pacific Islander | 1 (1)
Other / Not Provided | 34 (17)
Disease Characteristics, n (%)
ECOG PSa, n (%)
0 | 46 (23)
1 | 124 (62)
2 | 28 (14)
Relapsed AML, n (%) | 95 (48)
Refractory AML, n (%) | 104 (52)
IDH2 Mutationb, n (%)
R140 | 155 (78)
R172 | 44 (22)
Time from Initial AML Diagnosis (months)
Median (min, max) (172 patients) | 11.3 (1.2, 129.1)
Cytogenetic Risk Status, n (%)
Intermediate | 98 (49)
Poor | 54 (27)
Missing /Failure | 47 (24)
Prior Stem Cell Transplantation for AML, n (%) | 25 (13)
Transfusion Dependent at Baselinec, n (%) | 157 (79)
Number of Prior Anticancer Regimens, n (%)d
1 | 89 (45)
2 | 64 (32)
≥3 | 46 (23)
Median number of prior therapies (min, max) | 2 (1, 6)
ECOG PS: Eastern Cooperative Oncology Group Performance Status.
a 1 patient had missing baseline ECOG PS.
b For 3 patients with different mutations detected in bone marrow compared to blood, the result of blood is reported.
c Patients were defined as transfusion dependent at baseline if they received any red blood cell or platelet transfusions within the 8-week baseline period.
d Includes intensive and/or nonintensive therapies.

Efficacy was established on the basis of the rate of complete response (CR)/complete response with partial hematologic recovery (CRh), the duration of CR/CRh, and the rate of conversion from transfusion dependence to transfusion independence. The efficacy results are shown in Table 5 and were similar in both cohorts. The median follow-up was 6.6 months (range, 0.4 to 27.7 months). Similar CR/CRh rates were observed in patients with either R140 or R172 mutation.

Table 5: Efficacy Results in Patients with Relapsed or Refractory AML
Endpoint | IDHIFA (100 mg daily) N=199
CRa n (%) | 37 (19)
95% CI | (13, 25)
Median DORb (months) | 8.2
95% CI | (4.7, 19.4)
CRhc n (%) | 9 (4)
95% CI | (2, 8)
Median DOR (months) | 9.6
95% CI | (0.7, NA)
CR/CRh n (%) | 46 (23)
95% CI | (18, 30)
Median DOR (months) | 8.2
95% CI | (4.3, 19.4)
CI: confidence interval, NA: not available.
a CR (complete remission) was defined as <5% of blasts in the bone marrow, no evidence of disease, and full recovery of peripheral blood counts (platelets >100,000/microliter and absolute neutrophil counts [ANC] >1,000/microliter).
b DOR (duration of response) was defined as time since first response of CR or CRh to relapse or death, whichever is earlier.
c CRh (complete remission with partial hematological recovery) was defined as <5% of blasts in the bone marrow, no evidence of disease, and partial recovery of peripheral blood counts (platelets >50,000/microliter and ANC >500/microliter).

For patients who achieved a CR/CRh, the median time to first response was 1.9 months (range, 0.5 to 7.5 months) and the median time to best response of CR/CRh was 3.7 months (range, 0.6 to 11.2 months). Of the 46 patients who achieved a best response of CR/CRh, 39 (85%) did so within 6 months of initiating IDHIFA.

Among the 157 patients who were dependent on red blood cell (RBC) and/or platelet transfusions at baseline, 53 (34%) became independent of RBC and platelet transfusions during any 56-day post baseline period. Of the 42 patients who were independent of both RBC and platelet transfusions at baseline, 32 (76%) remained transfusion independent during any 56-day post baseline period.

16 HOW SUPPLIED/STORAGE AND HANDLING

How Supplied

50 mg tablet: Pale yellow to yellow oval-shaped film-coated tablet debossed “ENA” on one side and “50” on the other side.

- 30-count bottles of 50 mg tablets with a desiccant canister (NDC 59572-705-30)

100 mg tablet: Pale yellow to yellow capsule-shaped film-coated tablet debossed “ENA” on one side and “100” on the other side.

- 30-count bottles of 100 mg tablets with a desiccant canister (NDC 59572-710-30)

Storage

Store at 20°C-25°C (68°F-77°F); excursions permitted between 15°C-30°C (59°F-86°F) [see USP Controlled Room Temperature]. Keep the bottle tightly closed. Store and dispense in the original bottle (with a desiccant canister) to protect from moisture.

17 PATIENT COUNSELING INFORMATION

Advise the patient to read the FDA-approved patient labeling (Medication Guide).

Differentiation Syndrome

Advise patients on the risks of developing differentiation syndrome as early as 1 day and during the first 5 months on treatment. Ask patients to immediately report any symptoms suggestive of differentiation syndrome, such as fever, cough or difficulty breathing, bone pain, rapid weight gain or swelling of their arms or legs, to their healthcare provider for further evaluation [see Boxed Warning and Warnings and Precautions (5.1)].

Tumor Lysis Syndrome

Advise patients on the risks of developing tumor lysis syndrome. Advise patients on the importance of maintaining high fluid intake and the need for frequent monitoring of blood chemistry values [see Dosage and Administration (2.3) and Adverse Reactions (6.1)].

Gastrointestinal Adverse Reactions

Advise patients on risk of experiencing gastrointestinal reactions, such as diarrhea, nausea, vomiting, decreased appetite, and changes in their sense of taste. Ask patients to report these reactions to their healthcare provider, and advise patients how to manage them [see Adverse Reactions (6.1)].

Elevated Blood Bilirubin

Inform patients that taking IDHIFA may cause elevated blood bilirubin, which is due to its mechanism of action, and not due to liver damage. Advise patients to report any changes to the color of their skin or the whites of their eyes to their healthcare provider for further evaluation [see Adverse Reactions (6.1)].

Embryo-Fetal Toxicity

Advise pregnant women of the potential risk to a fetus. Advise females of reproductive potential to notify their healthcare provider of a known or suspected pregnancy [see Warnings and Precautions (5.2), Use in Specific Populations (8.1)].

Advise females of reproductive potential to use an effective non-hormonal contraceptive method during treatment with IDHIFA and for 2 months after the last dose. Advise males with female partners of reproductive potential to use effective contraception during treatment with IDHIFA and for 2 months after the last dose. Coadministration of IDHIFA may decrease the concentrations of combined hormonal contraceptives. [see Drug Interactions (7.1) and Use in Specific Populations (8.3)].

Lactation

Advise women not to breastfeed during treatment with IDHIFA and for 2 months after the last dose [see Use in Specific Populations (8.2)].

Drug Interactions

Advise patients to inform their healthcare providers of all concomitant products, including over-the-counter products and supplements [see Drug Interactions (7.1)].

Dosing and Storage Instructions

- Advise patients not to chew, split, or crush the tablets but swallow whole with a cup of water.
- Instruct patients that if they miss a dose or vomit after a dose of IDHIFA, to take it as soon as possible on the same day and return to normal schedule the following day. Advise patients not to take 2 doses to make up for the missed dose [see Dosage and Administration (2.2)].
- Keep IDHIFA in the original container. Keep the container tightly closed with desiccant canister inside to protect the tablets from moisture [see How Supplied/Storage and Handling (16)].

Marketed by:
Bristol-Myers Squibb Company
Princeton, NJ 08543 USA

Licensed from:
Servier Pharmaceuticals LLC
Boston, MA 02210

Trademarks are the property of their respective owners.

IDHIFA® is a trademark of Celgene Corporation, a Bristol Myers Squibb company.

Pat. https://www.bms.com/patient-and-caregivers/our-medicines.html

IDHPI.008/MG.007

MEDICATION GUIDE

IDHIFA® (eyed-HEE-fuh)

(enasidenib) tablets

What is the most important information I should know about IDHIFA?

IDHIFA may cause serious side effects, including:

- Differentiation Syndrome. Differentiation syndrome is a condition that affects your blood cells which may be life-threatening or lead to death if not treated. Differentiation syndrome has happened within 1 day and up to 5 months after starting IDHIFA. Call your healthcare provider or go to the nearest hospital emergency room right away if you develop any of the following symptoms of differentiation syndrome during treatment with IDHIFA:

- fever
- cough
- shortness of breath
- swelling of arms and legs

- swelling around neck, groin, or underarm area
- fast weight gain (greater than 10 pounds within a week)
- bone pain

If you develop any of these symptoms of differentiation syndrome, your healthcare provider may start you on a medicine taken by mouth or given through a vein (intravenous) called corticosteroids and may monitor you in the hospital.

What is IDHIFA?

IDHIFA is a prescription medicine used to treat people with acute myeloid leukemia (AML) with an isocitrate dehydrogenase-2 (IDH2) mutation whose disease has come back or has not improved after previous treatment(s).

It is not known if IDHIFA is safe and effective in children.

Before taking IDHIFA, tell your healthcare provider about all of your medical conditions, including if you:

- Are pregnant or plan to become pregnant. IDHIFA can cause harm to your unborn baby if taken during pregnancy.
  - If you are able to become pregnant, your healthcare provider will do a pregnancy test before you start taking IDHIFA.
  - Females who are able to become pregnant should use effective birth control (contraception) during treatment with IDHIFA and for 2 months after your last dose of IDHIFA.
  - IDHIFA may affect how hormonal contraceptives work and may cause them to not work as well. You should use an effective non-hormonal contraceptive method during treatment with IDHIFA and for 2 months after your last dose of IDHIFA if you use hormonal contraceptives.
  - Tell your healthcare provider right away if you become pregnant or think you might be pregnant during treatment with IDHIFA.
  - Males who have female partners that are able to become pregnant should use effective birth control during treatment with IDHIFA and for 2 months after your last dose of IDHIFA.
  - Talk to your healthcare provider about birth control methods that may be right for you during treatment with IDHIFA.
  - IDHIFA may cause fertility problems in females and males, which may affect your ability to have children. Talk to your healthcare provider if you have concerns about fertility.
- Are breastfeeding or plan to breastfeed. It is not known if IDHIFA passes into your breast milk. You should not breastfeed during your treatment with IDHIFA and for 2 months after your last dose of IDHIFA.

Tell your healthcare provider about all the medicines you take, including prescription and over-the-counter medicines, vitamins, and herbal supplements.

How should I take IDHIFA?

- Take IDHIFA exactly as your healthcare provider tells you to.
- Take IDHIFA 1 time a day at the same time each day.
- Swallow IDHIFA tablets whole. Do not chew, split, or crush IDHIFA tablets.
- Swallow IDHIFA with 8 ounces (one cup) of water.
- IDHIFA can be taken with or without food.
- If you miss a dose of IDHIFA or vomit after taking a dose of IDHIFA, take the dose of IDHIFA as soon as possible on the same day. Then take your next dose the next day at your regularly scheduled time. Do not take 2 doses at the same time to make up for the missed dose.
- Your healthcare provider should do blood tests to check your blood counts before you start IDHIFA treatment and at a minimum of every 2 weeks for at least the first 3 months during treatment to check for side effects.

What are the possible side effects of IDHIFA?

IDHIFA may cause serious side effects, including:

See “What is the most important information I should know about IDHIFA?”

The most common side effects of IDHIFA include:

- nausea
- vomiting
- diarrhea

- jaundice
- decreased appetite

Tell your healthcare provider if you have any changes to the color of your skin or the whites of your eyes.

Your healthcare provider will monitor you for side effects during treatment and may tell you to stop taking IDHIFA if you develop certain side effects.

These are not all the possible side effects of IDHIFA.

Call your doctor for medical advice about side effects. You may report side effects to FDA at 1‑800‑FDA-1088.

How should I store IDHIFA?

- Store IDHIFA at room temperature between 68°F to 77°F (20°C to 25°C).
- Keep IDHIFA in the original container.
- Keep the container tightly closed with desiccant canister inside to protect the tablets from moisture.

Keep IDHIFA and all medicines out of the reach of children.

General information about the safe and effective use of IDHIFA

Medicines are sometimes prescribed for purposes other than those listed in a Medication Guide. Do not take IDHIFA for conditions for which it was not prescribed. Do not give IDHIFA to other people, even if they have the same symptoms you have. It may harm them. You can ask your pharmacist or healthcare provider for information about IDHIFA that is written for health professionals.

What are the ingredients in IDHIFA?

Active ingredient: enasidenib

Inactive ingredients: colloidal silicon dioxide, hydroxypropyl cellulose, hypromellose acetate succinate, iron oxide yellow, magnesium stearate, microcrystalline cellulose, polyethylene glycol, polyvinyl alcohol, sodium lauryl sulfate, sodium starch glycolate, talc, and titanium dioxide

Marketed by: Bristol-Myers Squibb Company, Princeton, NJ 08543 USA

Licensed from: Servier Pharmaceuticals LLC, Boston, MA 02210

IDHIFA® is a trademark of Celgene Corporation, a Bristol Myers Squibb company.

Pat. https://www.bms.com/patient-and-caregivers/our-medicines.html

IDHMG.007

For more information go to www.IDHIFA.com or call 1-800-721-5072.

This Medication Guide has been approved by the U.S. Food and Drug Administration.
Revised: 1/2025

PRINCIPAL DISPLAY PANEL - 50 mg Tablet Bottle Label

NDC 59572-705-30

IDHIFA®
(enasidenib) tablets

50 mg

Dispense in original
container with desiccant.

Swallow whole, do not
chew or split tablets.

Rx only
30 Tablets

PRINCIPAL DISPLAY PANEL - 100 mg Tablet Bottle Label

NDC 59572-710-30

IDHIFA®
(enasidenib) tablets

100 mg

Dispense in original
container with desiccant.

Swallow whole, do not
chew or split tablets.

Rx only
30 Tablets